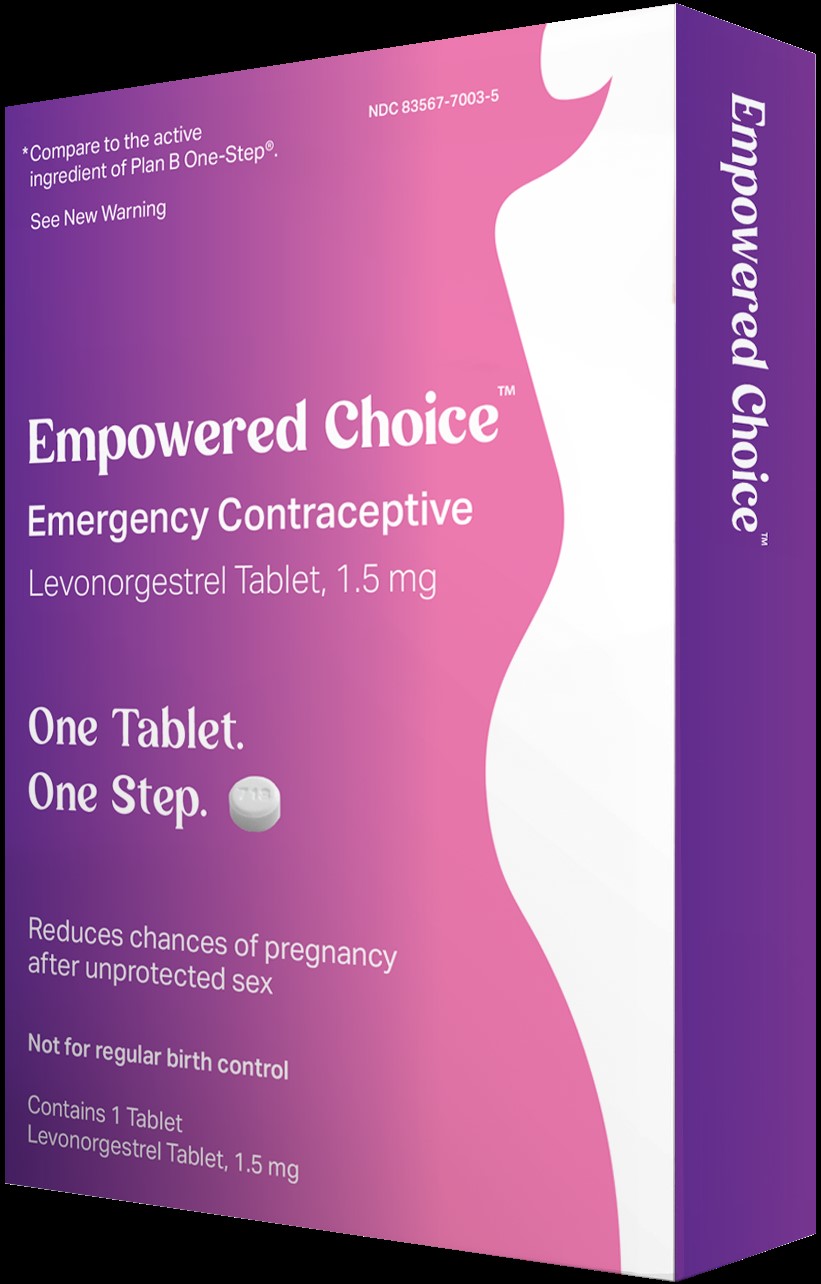 DRUG LABEL: Empowered Choice
NDC: 83567-7003 | Form: TABLET
Manufacturer: Versea Diagnostics
Category: otc | Type: HUMAN OTC DRUG LABEL
Date: 20230726

ACTIVE INGREDIENTS: LEVONORGESTREL 1.5 mg/1 1
INACTIVE INGREDIENTS: STARCH, CORN; HYPROMELLOSE, UNSPECIFIED; LACTOSE MONOHYDRATE; MAGNESIUM STEARATE; SILICON DIOXIDE; TALC

ACTIVE INGREDIENT

Levonorgestrel, USP 1.5 mg

PURPOSE

Emergency Contraceptive

USE

for women to reduce chance of pregnancy af ter unprotected sex (if a contraceptive failed or if you did not use bir th control)

WARNINGS

Allergy alert

Do not use if you have ever had an allergic reaction to levonorgestrel.

Sexually transmitted diseases (STDs) alert

This product does not protect against HIV/AIDS or other STDs.

Do not use

• if you are already pregnant (because it will not work)
• for regular birth control

Ask a doctor or pharmacist before use if you are taking efavirenz (HIV medication) or rifampin (tuberculosis treatment) or medication for seizures (epilepsy). These medications may reduce the effectiveness of levonorgestrel.

When using this product you may have

• menstrual changes
• tiredness

• breast pain
• nausea
• headache

• vomiting

• lower stomach (abdominal) pain

• dizziness

Keep out of reach of children. In case of overdose, get medical help or contact a Poison Control Center right away (1-800-222-1222).

DIRECTIONS

• take as soon as possible within 72 hours (3 days) after unprotected sex. The sooner you take it, the better it will work.
• if you vomit within 2 hours after taking the medication, call a healthcare professional to find out if you should repeat the dose

OTHER INFORMATION

• read the instructions, warnings, and enclosed product leaflet before use
• this product works mainly by preventing ovulation (egg release). It may also prevent fertilization of a released egg (joining of sperm and egg) or attachment of a fertilized egg to the uterus (implantation).
• do not use if carton is open or tear strip is removed or blister seal is broken or missing
• store at 20° to 25°C (68° to 77°F)

INACTIVE INGREDIENTS

colloidal silicon dioxide, corn starch, hypromellose, lactose monohydrate, magnesium stearate, talc

QUESTIONS?

Call 1-800-397-0670

SPL UNCLASSIFIED SECTION

Distributed by:

Versea Diagnostics, LLC

Tampa, FL 33602

PRINCIPAL DISPLAY PANEL

NDC 83567-7003-5

*Compare to the active ingredient of Plan B One-Step®

EMPOWERED CHOICETM

Levonorgestrel Tablet 1.5 mg

Emergency Contraceptive

1 Tablet Levonorgestrel 1.5 mg

One Tablet. One Step.

- Reduces the chance of pregnancy after unprotected sex
- Not for regular birth control
- The sooner you take it, the more effective it will be
- Take as soon as possible within 72 hours (3 days) after unprotected sex
- Will not harm an existing pregnancy